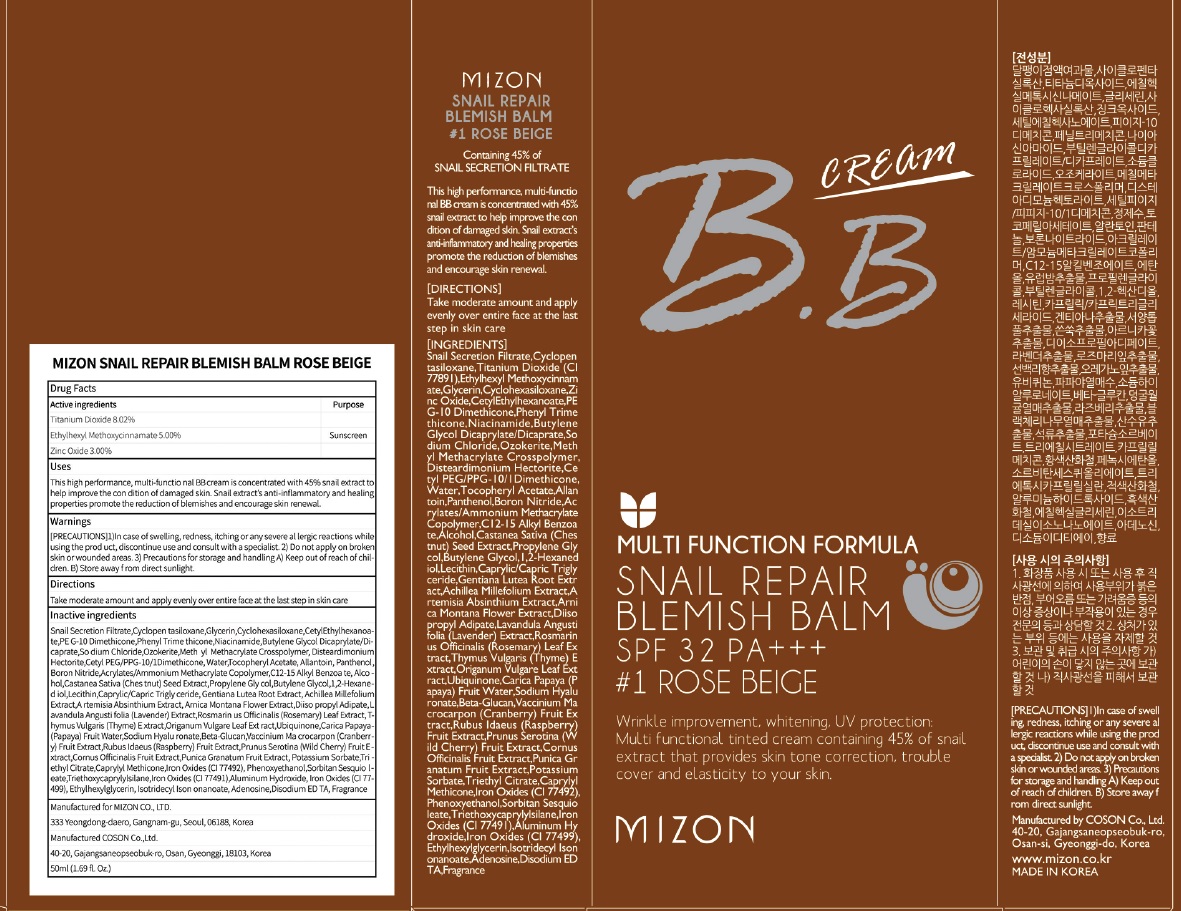 DRUG LABEL: MIZON SNAIL REPAIR BLEMISH BALM ROSE BEIGE
NDC: 57718-250 | Form: CREAM
Manufacturer: MIZON CO.,LTD.
Category: otc | Type: HUMAN OTC DRUG LABEL
Date: 20180724

ACTIVE INGREDIENTS: Titanium Dioxide 4.01 g/50 mL; Octinoxate 2.50 g/50 mL; Zinc Oxide 1.50 g/50 mL
INACTIVE INGREDIENTS: Glycerin; Phenyl Trimethicone

ACTIVE INGREDIENT

Active ingredients: Titanium Dioxide 8.02%, Ethylhexyl Methoxycinnamate 5.00%, Zinc Oxide 3.00%

INACTIVE INGREDIENT

Inactive ingredients:

Snail Secretion Filtrate,Cyclopen tasiloxane,Glycerin,Cyclohexasiloxane,CetylEthylhexanoate,PE G-10 Dimethicone,Phenyl Trime thicone,Niacinamide,Butylene Glycol Dicaprylate/Dicaprate,So dium Chloride,Ozokerite,Meth yl Methacrylate Crosspolymer, Disteardimonium Hectorite,Ce tyl PEG/PPG-10/1Dimethicone, Water,Tocopheryl Acetate,Allan toin,Panthenol,Boron Nitride,Ac rylates/Ammonium Methacrylate Copolymer,C12-15 Alkyl Benzoa te,Alcohol,Castanea Sativa (Ches tnut) Seed Extract,Propylene Gly col,Butylene Glycol,1,2-Hexaned iol,Lecithin,Caprylic/Capric Trigly ceride,Gentiana Lutea Root Extr act,Achillea Millefolium Extract,A rtemisia Absinthium Extract,Arni ca Montana Flower Extract,Diiso propyl Adipate,Lavandula Angusti folia (Lavender) Extract,Rosmarin us Officinalis (Rosemary) Leaf Ex tract,Thymus Vulgaris (Thyme) E xtract,Origanum Vulgare Leaf Ext ract,Ubiquinone,Carica Papaya (P apaya) Fruit Water,Sodium Hyalu ronate,Beta-Glucan,Vaccinium Ma crocarpon (Cranberry) Fruit Ex tract,Rubus Idaeus (Raspberry) Fruit Extract,Prunus Serotina (W ild Cherry) Fruit Extract,Cornus Officinalis Fruit Extract,Punica Gr anatum Fruit Extract,Potassium Sorbate,Triethyl Citrate,Caprylyl Methicone,Iron Oxides (CI 77492), Phenoxyethanol,Sorbitan Sesquio leate,Triethoxycaprylylsilane,Iron Oxides (CI 77491),Aluminum Hy droxide,Iron Oxides (CI 77499), Ethylhexylglycerin,Isotridecyl Ison onanoate,Adenosine,Disodium ED TA,Fragrance

PURPOSE

Purpose: Sunscreen

WARNINGS

[PRECAUTIONS]

1)In case of swell ing, redness, itching or any severe al lergic reactions while using the prod uct, discontinue use and consult with a specialist. 2) Do not apply on broken skin or wounded areas. 3) Precautions for storage and handling A) Keep out of reach of children. B) Store away f rom direct sunlight.

KEEP OUT OF REACH OF CHILDREN

DESCRIPTION

Uses:

This high performance, multi-functio nal BB cream is concentrated with 45% snail extract to help improve the con dition of damaged skin. Snail extract’s anti-inflammatory and healing properties promote the reduction of blemishes and encourage skin renewal.

Directions:

Take moderate amount and apply evenly over entire face at the last step in skin care